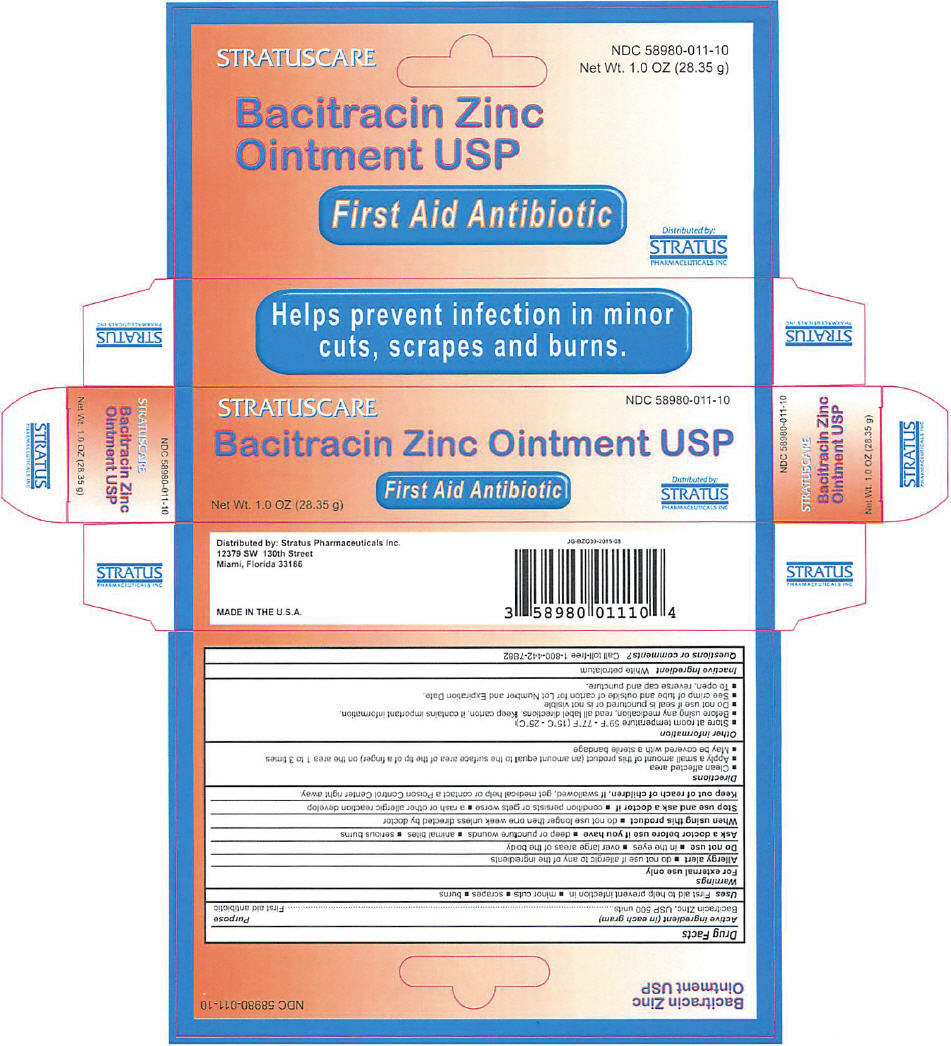 DRUG LABEL: BACITRACIN ZINC
NDC: 58980-011 | Form: OINTMENT
Manufacturer: STRATUS PHARMACEUTICALS INC
Category: otc | Type: HUMAN OTC DRUG LABEL
Date: 20241031

ACTIVE INGREDIENTS: BACITRACIN ZINC 500 [USP'U]/1 g
INACTIVE INGREDIENTS: PETROLATUM

BACITRACIN ZINC

Drug Facts

Active ingredient (in each gram)

Bacitracin Zinc, USP 500 units

Purpose

First aid antibiotic

Uses

First aid to help prevent infection in

- minor cuts
- scrapes
- burns

Warnings

For external use only

Allergy alert

- do not use if allergic to any of the ingredients

Do not use

- in the eyes
- over large areas of the body

Ask a doctor before use if you have

- deep or puncture wounds
- animal bites
- serious burns

When using this product

- do not use longer then one week unless directed by doctor

Stop use and ask a doctor if

- condition persists or gets worse
- a rash or other allergic reaction develop

Keep out of reach of children. If swallowed, get medical help or contact a Poison Control Center right away.

Directions

- Clean affected area
- Apply a small amount of this product (an amount equal to the surface area of the tip of a finger) on the area 1 to 3 times
- May be covered with a sterile bandage

Other information

- Store at room temperature 59°F - 77°F (15°C - 25°C)
- Before using any medication, read all label directions. Keep carton, it contains important information.
- Do not use if seal is punctured or is not visible
- See crimp of tube and outside of carton for Lot Number and Expiration Date.
- To open, reverse cap and puncture.

Inactive Ingredient

White petrolatum

Questions or comments?

Call toll-free 1-800-442-7882

Distributed by: Stratus Pharmaceuticals Inc.
12379 SW 130th Street
Miami, Florida 33186

PRINCIPAL DISPLAY PANEL - 28.35 g Tube Box

STRATUSCARE
NDC 58980-011-10

Bacitracin Zinc Ointment USP

First Aid Antibiotic

Net Wt. 1.0 OZ (28.35 g)

Distributed by:
STRATUS
PHARMACEUTICALS INC